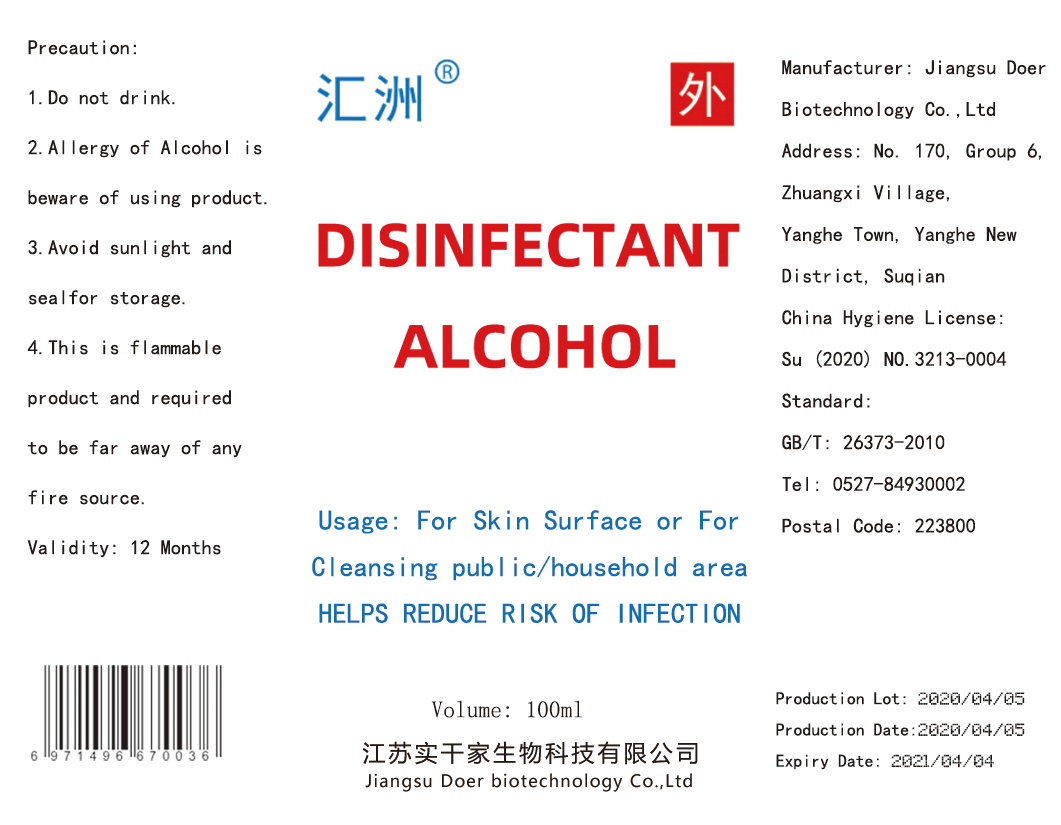 DRUG LABEL: DISINFECTANT ALCOHOL
NDC: 55449-001 | Form: LIQUID
Manufacturer: Jiangsu Doer biotechnology Co., Ltd
Category: otc | Type: HUMAN OTC DRUG LABEL
Date: 20201103

ACTIVE INGREDIENTS: ALCOHOL 75 mL/100 mL
INACTIVE INGREDIENTS: WATER

55449-001 outcome

PURPOSE

Disinfection
Sterilization
No Rinseing

DOSAGE AND ADMINISTRATION

This is flammable product and required to be far away of any fire source.

WARNINGS

Do not drink.
Allergy of Alcohol is beware of us ing product. Avoid sunlight and seal for storage.

ACTIVE INGREDIENT

alcohol

INACTIVE INGREDIENT

water

keep out of reach of children

INDICATIONS AND USAGE

For Skin Surface or For Cleansing publ ic/household area
HELPS REDUCE RISK OF INFECTION